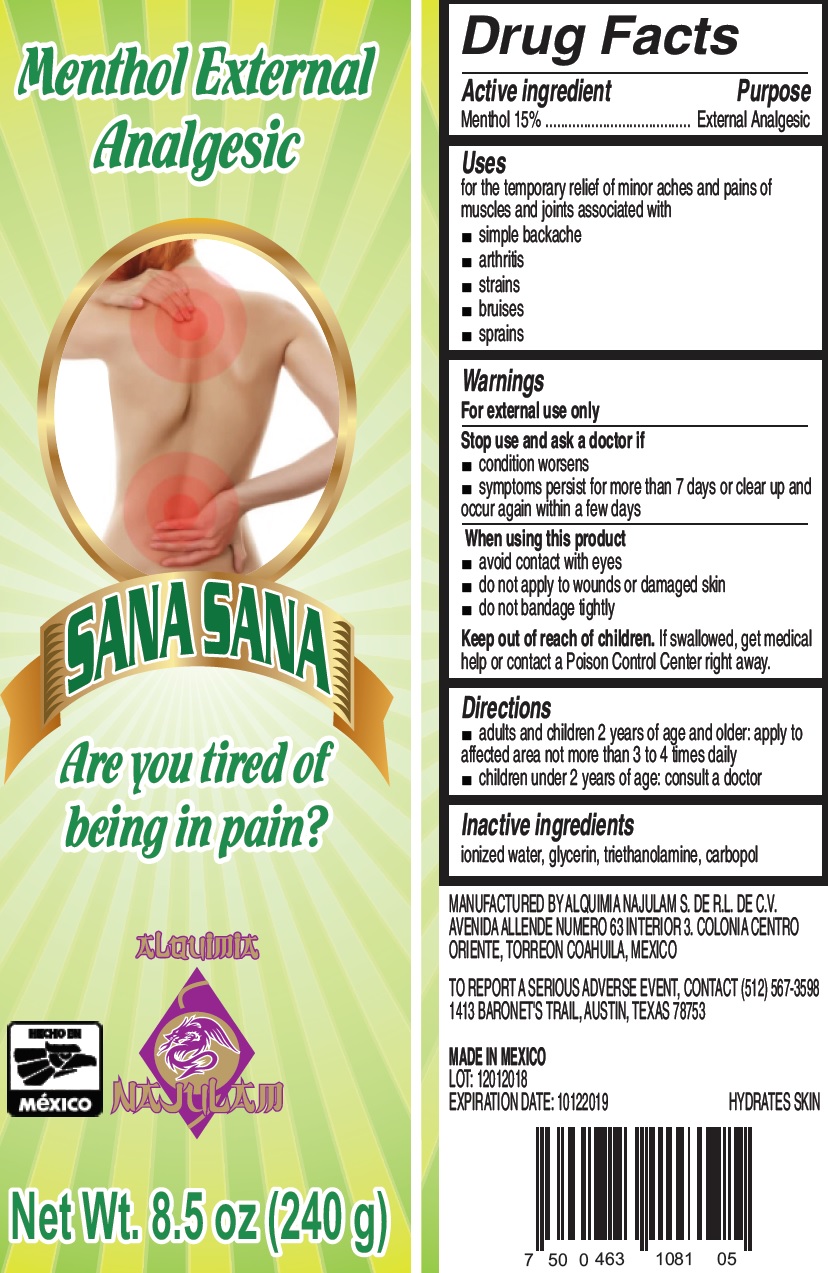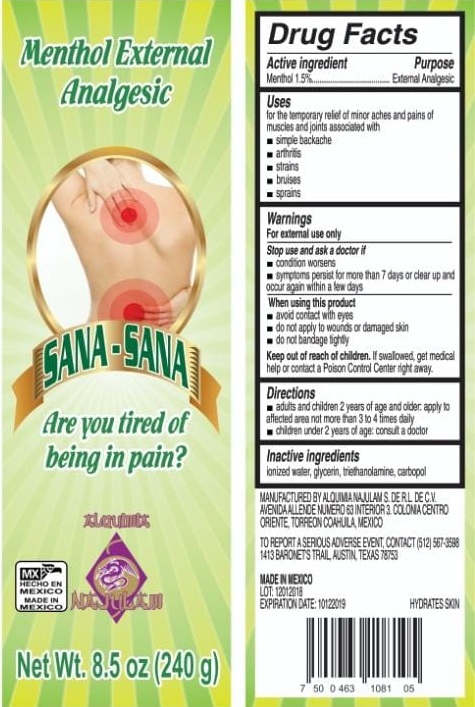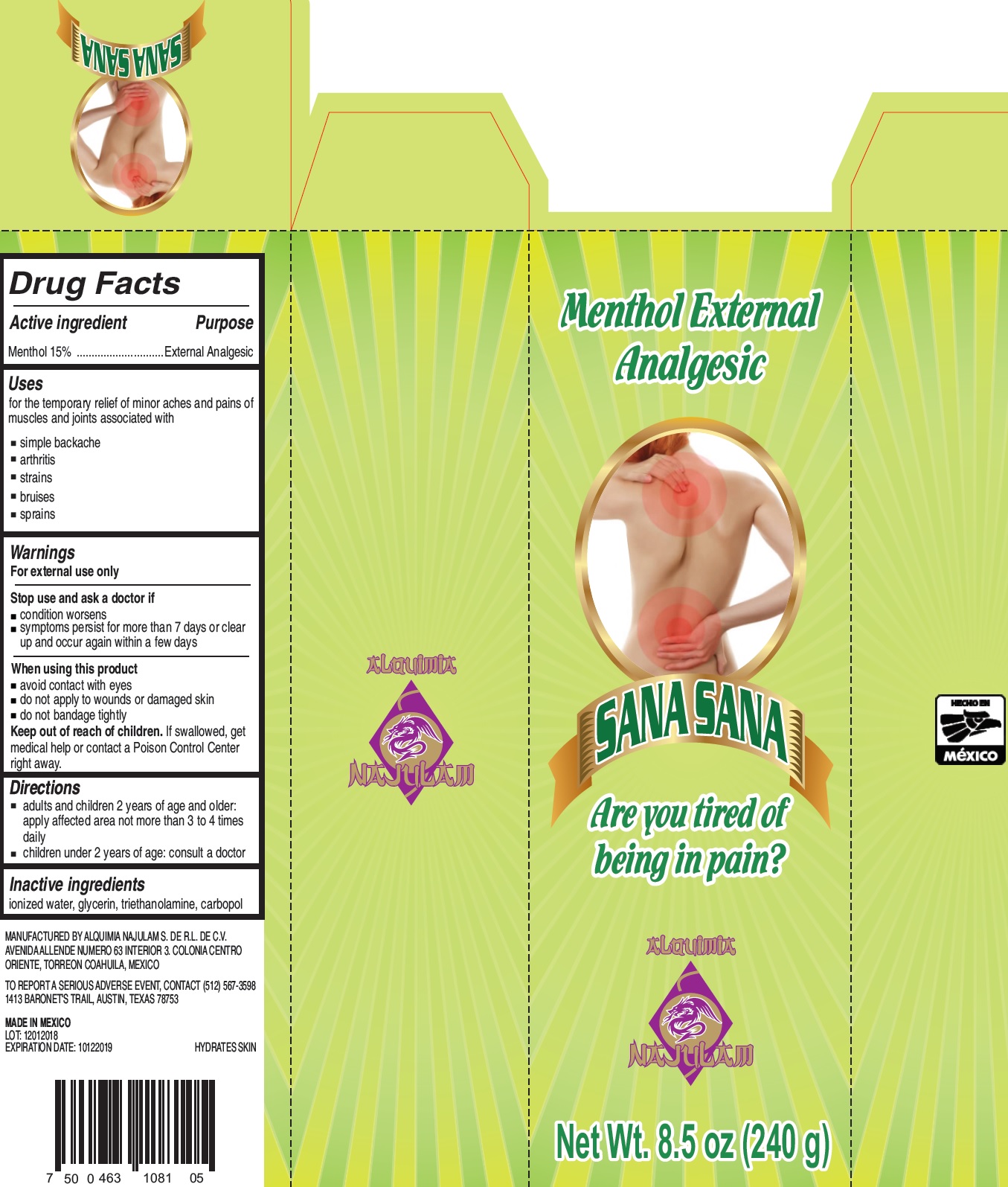 DRUG LABEL: SANA SANA Menthol External Analgesic
NDC: 72367-000 | Form: GEL
Manufacturer: Alquimia Najulam S de RL de CV
Category: otc | Type: HUMAN OTC DRUG LABEL
Date: 20250725

ACTIVE INGREDIENTS: MENTHOL 150 mg/1 g
INACTIVE INGREDIENTS: WATER; GLYCERIN; TROLAMINE; CARBOXYPOLYMETHYLENE

SANA SANA Menthol External Analgesic

Active ingredient

Menthol 15%

Purpose

External Analgesic

Uses

for the temporary relief of minor aches and pains of muscles and joints associated with
• simple backache
• arthritis
• strains
• bruises
• sprains

Warnings

For external use only

Stop use and ask a doctor if

• condition worsens

• symptoms persist for more than 7 days or clear up and occur again within a few days

When using this product

• avoid contact with eyes

• do not apply to wounds or damaged skin

• do not bandage tightly

Keep out of reach of children.

If swallowed, get medical help or contact a Poison Control Center right away.

Directions

• adults and children 2 years of age and older: apply to affected area not more than 3 to 4 times daily

• children under 2 years of age: consult a doctor

Inactive ingredients

ionized water, glycerin, triethanolamine, carbopol